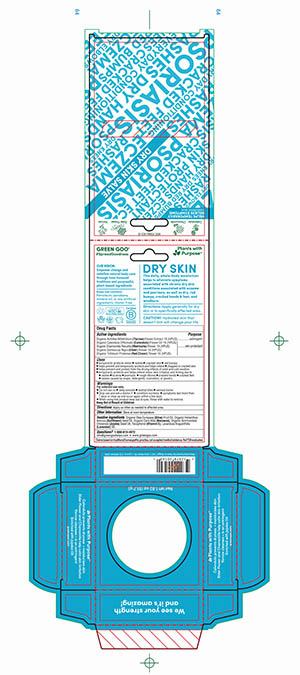 DRUG LABEL: Dry Skin Care
NDC: 70994-103 | Form: SALVE
Manufacturer: Spry Life LLC
Category: homeopathic | Type: HUMAN OTC DRUG LABEL
Date: 20251215

ACTIVE INGREDIENTS: CALENDULA OFFICINALIS FLOWER 1 [hp_X]/51.7 g; CHAMOMILE 1 [hp_X]/51.7 g; TRIFOLIUM PRATENSE FLOWER 1 [hp_X]/51.7 g; SAMBUCUS NIGRA FLOWER 1 [hp_X]/51.7 g; ACHILLEA MILLEFOLIUM 1 [hp_X]/51.7 g; VIOLA TRICOLOR 1 [hp_X]/51.7 g
INACTIVE INGREDIENTS: YELLOW WAX; ALPHA-TOCOPHEROL; LAVENDER OIL; OLIVE OIL; SUNFLOWER OIL; JOJOBA OIL

Dry Skin Care

Purpose Section

Skin Protectant

Astringent

Active Ingredients

OrganicAchilleaMillefolium(Yarrow)FlowerExtract1X(HPUS)

Organic Calendula Officinalis (Calendula) Flower Oil 1X (HPUS)

OrganicChamomillaRecutita(Matricaria)Flower 1X(HPUS)

Organic Sambucus Nigra (Elder) Flower 1X (HPUS)

Organic Trifolium Pratense (Red Clover) Flower 1X (HPUS)

Indications & Usage

■ temporarily protects minor ■ rashes ■ cracked skin ■ red bumps
■ helps prevent and temporarily protects and helps relieve ■ chapped or cracked skin

■ helps prevent and protect from the drying effects of wind and cold weather
■ temporarily protects and helps relieve minor skin irritation and itching due to

■ rashes ■ eczema ■ psoriasis ■ rough elbows ■ cracked hands ■ cracked feet

■ rashes caused by soaps, detergents, cosmetics, or jewelry

Keep out of reach of children section

Keep out of reach of children.

Warnings Section

Warnings

For external use only.

■ Do not use on ■ on deep wounds ■ animal bites ■ serious burns
■ Stop use and ask a doctor if ■ condition worsens ■ symptoms last more than

7 days or clear up and occur again within a few days
■ When using this product keep out of eyes. Rinse with water to remove.

Storage

Store at room temperature.

Dosage & Administration Section

Apply as often as needed to affected area.

Inactive Ingredients

Organic Olea Europaea (Olive) Fruit Oil, Organic Helianthus Annuus (Sunflower) Seed Oil, Organic Cera Alba (Beeswax), Organic Simmondsia Chinensis (Jojoba) Seed Oil, Tocopherol (Vitamin E), Lavandula Angustifolia (Lavender) Oil.